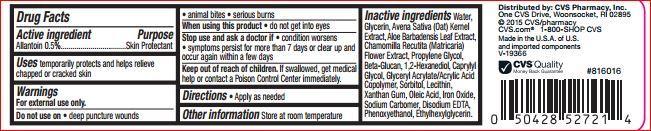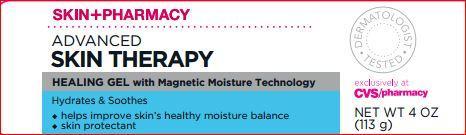 DRUG LABEL: Healing
NDC: 59779-436 | Form: GEL
Manufacturer: CVS
Category: otc | Type: HUMAN OTC DRUG LABEL
Date: 20171208

ACTIVE INGREDIENTS: Allantoin 0.5 g/100 g
INACTIVE INGREDIENTS: Water; Glycerin; OAT; ALOE VERA LEAF; CHAMOMILE; Propylene Glycol; CURDLAN; 1,2-Hexanediol; Caprylyl Glycol; Sorbitol; LECITHIN, SOYBEAN; Xanthan Gum; Oleic Acid; FERRIC OXIDE RED; EDETATE DISODIUM; Phenoxyethanol; Ethylhexylglycerin

Drug Facts

Active ingredient Purpose

Allantoin 0.5%.................................Skin Protectant

Uses

temporarily protects and helps relieve chapped or cracked skin

Warning

For external use only.
Do not use on • deep puncture wounds• animal bites • serious burns

When using this product • do not get into eyes

Stop use and ask a doctor if • condition worsens • symptoms persist for more than 7 days or clear up and occur again within a few days

Keep out of reach of children. If swallowed, get medical help or contact a Poison Control Center immediately.

DOSAGE AND ADMINISTRATION

Directions • Apply as needed

Other information Store at room temperature

Inactive ingredients

Water, Glycerin, Avena Sativa (Oat) Kernel Extract, Aloe Barbadensis Leaf Extract, Chamomilla Recutita (Matricaria) Flower Extract, Propylene Glycol, Beta-Glucan, 1,2-Hexanediol, Caprylyl Glycol, Glyceryl Acrylate/Acrylic Acid Copolymer, Sorbitol, Lecithin, Xanthan Gum, Oleic Acid, Iron Oxide, Sodium Carbomer, Disodium EDTA, Phenoxyethanol, Ethylhexylglycerin